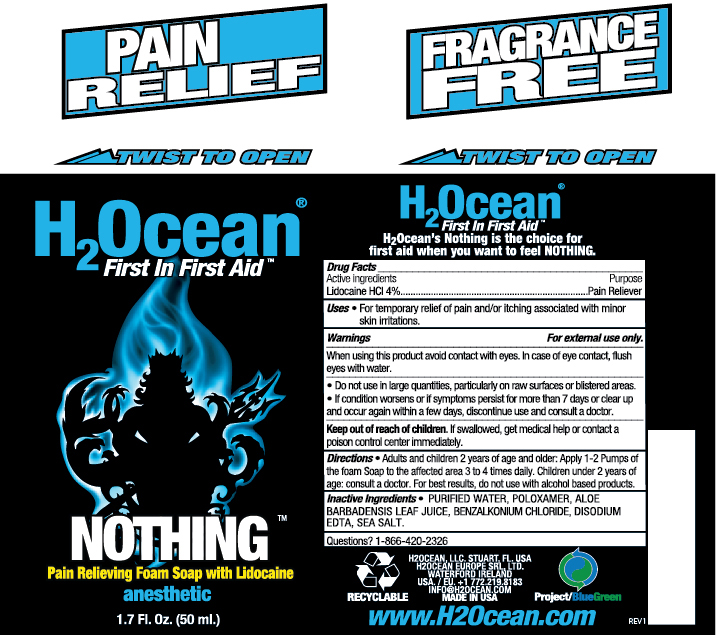 DRUG LABEL: Nothing
NDC: 70411-102 | Form: LIQUID
Manufacturer: H2Ocean, LLC
Category: otc | Type: HUMAN OTC DRUG LABEL
Date: 20231030

ACTIVE INGREDIENTS: LIDOCAINE 4 g/100 mL
INACTIVE INGREDIENTS: WATER; POLOXAMER 124; ALOE VERA LEAF; BENZALKONIUM CHLORIDE; DISODIUM ETHYLENEDIAMINEDIACETATE; SODIUM CHLORIDE

Active Ingredient

Lidocane hydrochloride, 4%

Purpose

Pain reliever

Uses

For the temporary relief of pain and/or itching associated with minor skin irritations

Warnings

For external use only

When using this product avoid contact with the eyes. In case of eye contact, flush eyes with water.

Do not use in large quantities, particularly on raw surfaces of blistered areas.

STOP USE

If condition worsens or if symptoms persist for more than 7 days or clear up and occur again within a few days, discontinue use and consult a doctor.

Keep out of reach of children. If swallowed, get medical help or contact a poison control center immediately.

Directions

Adults and children 2 years of age and older: Apply 1-2 pumps of the foam soap to the affected area 3-4 times daily.

Children under 2 years of age: consult a doctor.

For best results, do not use with alcohol based products.

Inactive Ingredients

Purified water, Poloxamer, Aloe Barbadensis Leaf Juice, Benzalkonium Chloride, Disodium ETDA, Sea Salt

Questions? 1-888-420-2326

H2Ocean (r)

First In First Aid (TM)

H2Ocean's Nothing is the choice for first aid when ou want to feel NOTHING.

H2Ocean, LLC, Stuart, FL, USA

H2Ocean Europe SRL LTD., Waterford, Ireland

USA / EU +1 772.219.8183

Info@H2Ocean.com

Made in USA

www.H2Ocean.com

PACKAGE LABEL

H2Ocean(r)

First In First Aid (TM)

NOTHING (TM)

Pain Relieving Soap with Lidocaine

Anesthetic

1.7 Fl. Oz. (50 ml.)